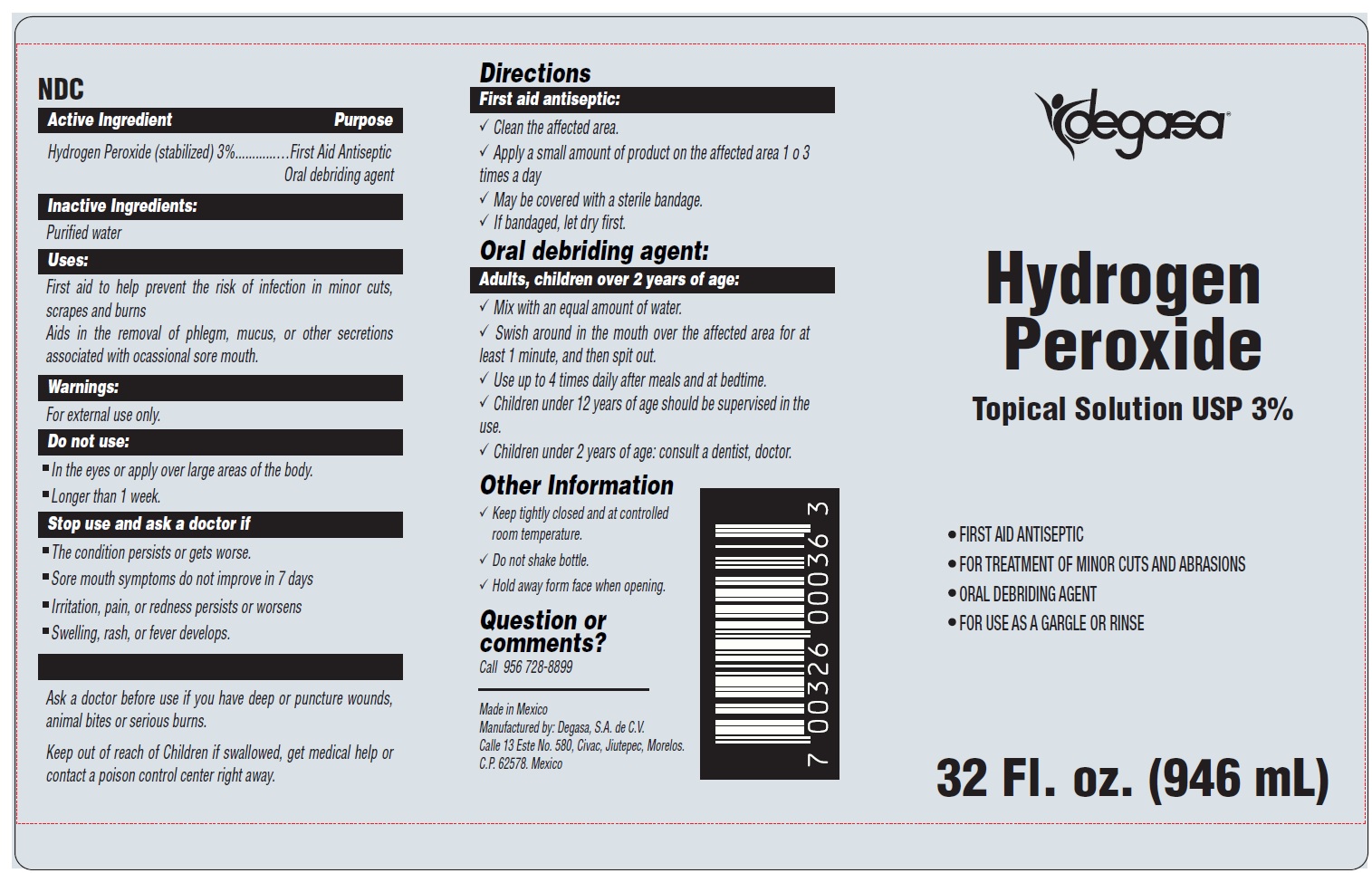 DRUG LABEL: HYDROGEN PEROXIDE
NDC: 67326-354 | Form: LIQUID
Manufacturer: DEGASA SA DE CV
Category: otc | Type: HUMAN OTC DRUG LABEL
Date: 20231105

ACTIVE INGREDIENTS: HYDROGEN PEROXIDE 0.3 mL/1 mL
INACTIVE INGREDIENTS: WATER

HYDROGEN PEROXIDE TOPICAL SOLUTION USP

Active Ingredient

Hydrogen Peroxide (stabilized) 3%

Purpose

First Aid Antiseptic Oral debriding agent

Inactive Ingredients:

Purified water

Uses:

First aid to help prevent the risk of infection in minor cuts, scrapes and burns Aids in the removal of phlegm, mucus, or other secretions associated with ocassional sore mouth.

Warnings:

For external use only.

Do not use:

- In the eyes or apply over large areas of the body.
- Longer than 1 week.

Stop use and ask a doctor if

- The condition persists or gets worse.
- Sore mouth symptoms do not improve in 7 days
- Irritation, pain, or redness persists or worsens
- Swelling, rash, or fever develops.

Ask a doctor before use if you have deep or puncture wounds, animal bites or serious burns.

Keep out of reach of Children if swallowed, get medical help or contact a poison control center right away.

Directions

First aid antiseptic:

√ Clean the affected area.

√ Apply a small amount of product on the affected area 1 o 3 times a day

√ May be covered with a sterile bandage.

√ If bandaged, let dry first.

Oral debriding agent:

Adults, children over 2 years of age:

√ Mix with an equal amount of water.

√ Swish around in the mouth over the affected area for at least 1 minute, and then spit out.

√ Use up to 4 times daily after meals and at bedtime.

√ Children under 12 years of age should be supervised in the use.

√ Children under 2 years of age: consult a dentist, doctor.

Other Information

√ Keep tightly closed and at controlled room temperature.

√ Do not shake bottle.

√ Hold away form face when opening.

Question or comments?

Call 956 728-8899